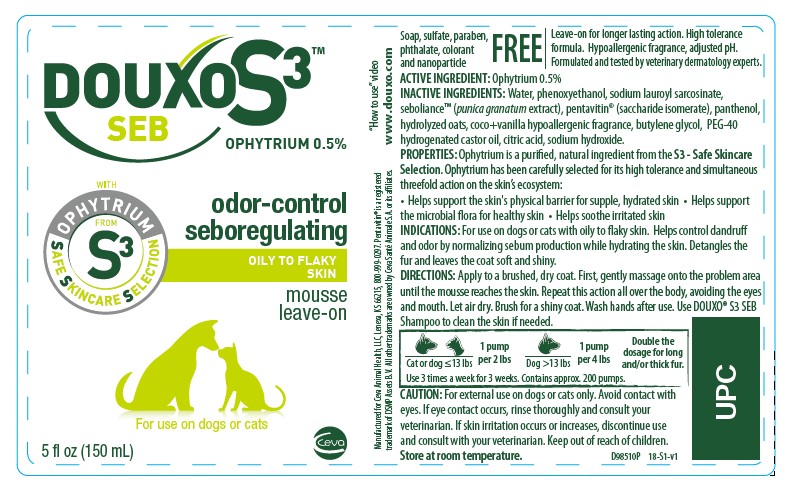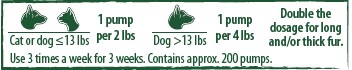 DRUG LABEL: DOUXO S3
NDC: 13744-155 | Form: LIQUID
Manufacturer: Ceva Sante Animale
Category: animal | Type: OTC ANIMAL DRUG LABEL
Date: 20250312

ACTIVE INGREDIENTS: OPHIOPOGON JAPONICUS ROOT 5.0 mg/1 mL
INACTIVE INGREDIENTS: PHENOXYETHANOL; PUNICA GRANATUM SEED OIL; SACCHARIDE ISOMERATE; OAT; BUTYLENE GLYCOL; PEG-40 CASTOR OIL; CITRIC ACID MONOHYDRATE; SODIUM HYDROXIDE

DOUXO S3™ SEB

mousse

OPHYTRIUM 0.5%

Soap, sulfate, paraben, phthalate, colorant and nanoparticle FREE

Leave-on for longer lasting action. High tolerance formula. Hypoallergenic fragrance, adjusted pH. Formulated and tested by veterinary dermatology experts.

ACTIVE INGREDIENT: Ophytrium 0.5%

INACTIVE INGREDIENT

INACTIVE INGREDIENTS: Water, phenoxyethanol, sodium lauroyl sarcosinate, seboliance™ (punica granatum extract), pentavitin® (saccharide isomerate), panthenol, hydrolyzed oats, coco+vanilla hypoallergenic fragrance, butylene glycol, PEG-40 hydrogenated castor oil, citric acid, sodium hydroxide.

DESCRIPTION

PROPERTIES: Ophytrium is a purified, natural ingredient from the S3 - Safe Skincare Selection. Ophytrium has been carefully selected for its high tolerance and simultaneous threefold action on the skin’s ecosystem: • Helps support the skin's physical barrier for supple, hydrated skin • Helps support the microbial flora for healthy skin • Helps soothe irritated skin

INDICATIONS AND USAGE

INDICATIONS: For use on dogs or cats with oily to flaky skin. Helps control dandruff and odor by normalizing sebum production while hydrating the skin. Detangles the fur and leaves the coat soft and shiny.

DIRECTIONS: Apply to a brushed, dry coat. First, gently massage onto the problem area until the mousse reaches the skin. Repeat this action all over the body, avoiding the eyes and mouth. Let air dry. Brush for a shiny coat. Wash hands after use. Use DOUXO® S3 SEB
Shampoo to clean the skin if needed.

PRECAUTIONS

CAUTION: For external use on dogs or cats only. Avoid contact with eyes. If eye contact occurs, rinse thoroughly and consult your veterinarian. If skin irritation occurs or increases, discontinue use and consult with your veterinarian. Keep out of reach of children.

STORAGE AND HANDLING

Store at room temperature.

“How to use” video www.douxo.com

Manufactured for Ceva Animal Health, LLC, Lenexa, KS 66215, 800-999-0297
Pentavitin® is a registered trademark of DSMP Assets B.V.
All other trademarks are owned by Ceva Santé Animale S.A. or its affiliates.

PRINCIPAL DISPLAY PANEL - 200 mL Bottle

DOUXO S3™

SEB

OPHYTRIUM 0.5%

odor-controlseboregulating

OILY TO FLAKY SKIN

moussse leave-on

For use on dogs or cats

5 fl oz (150 mL)